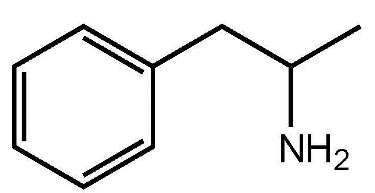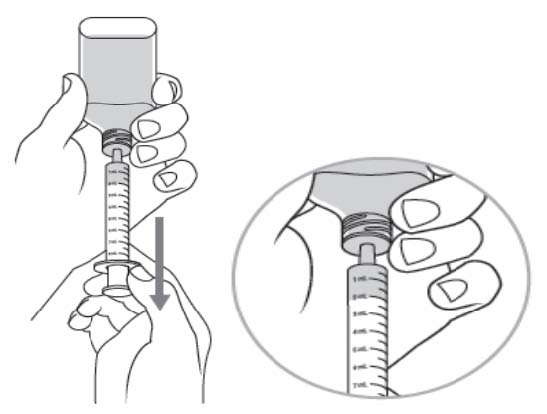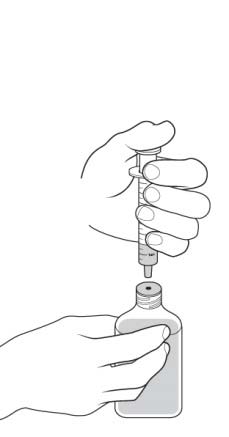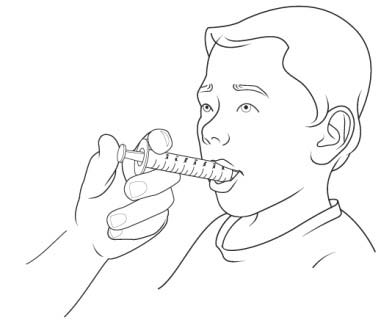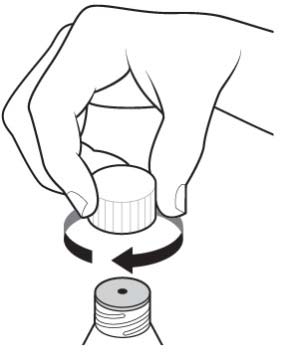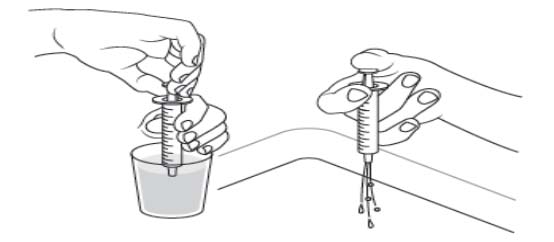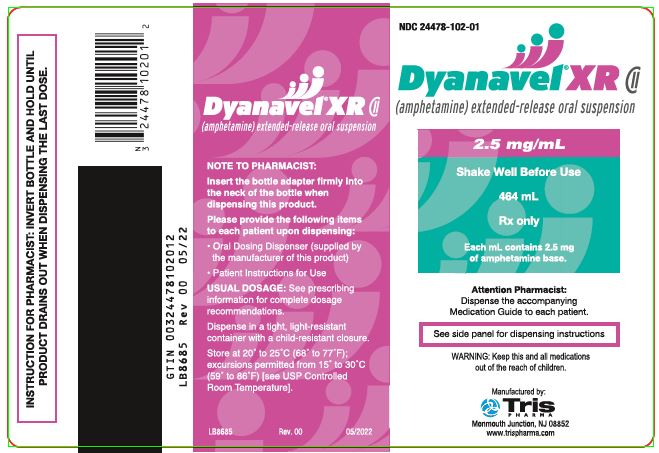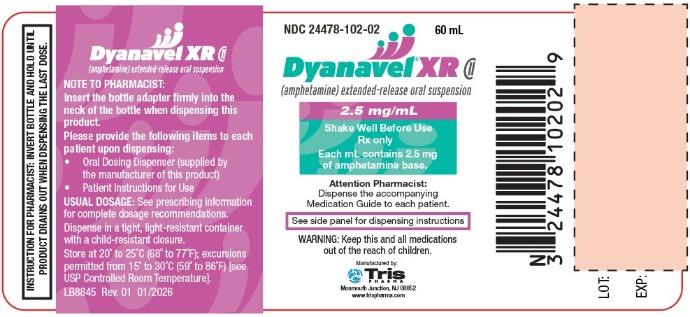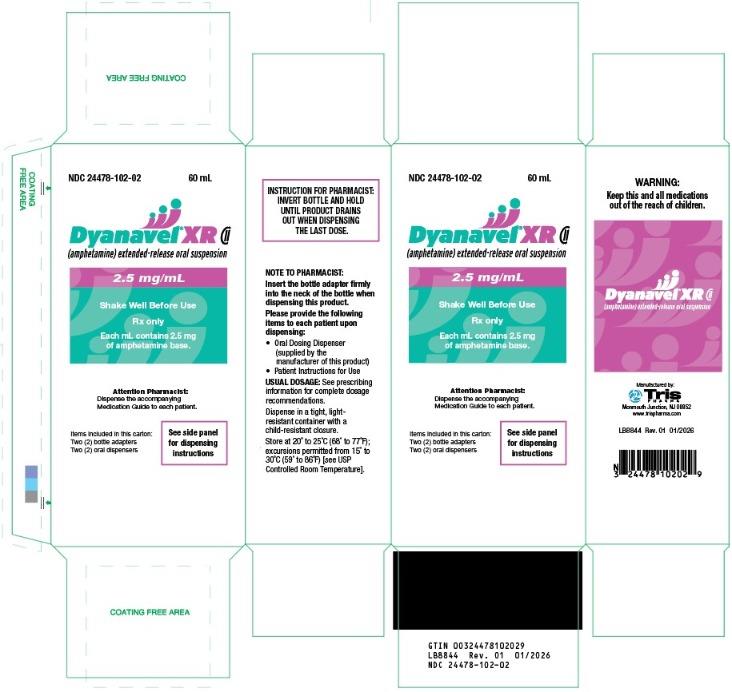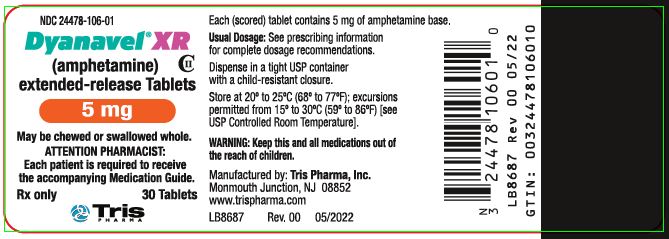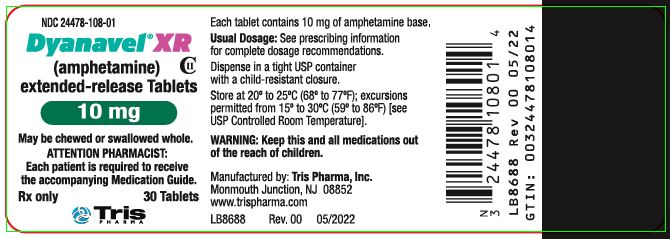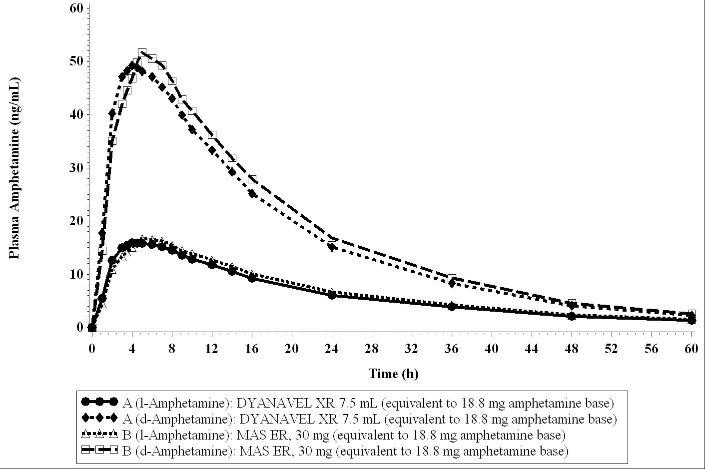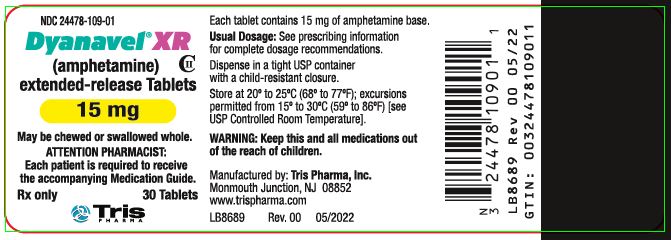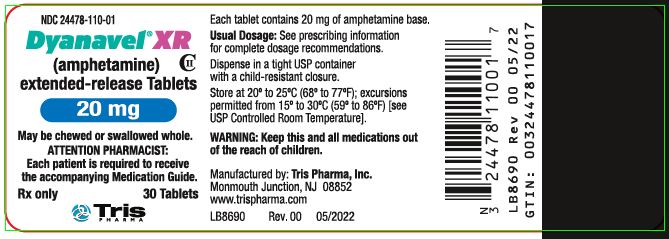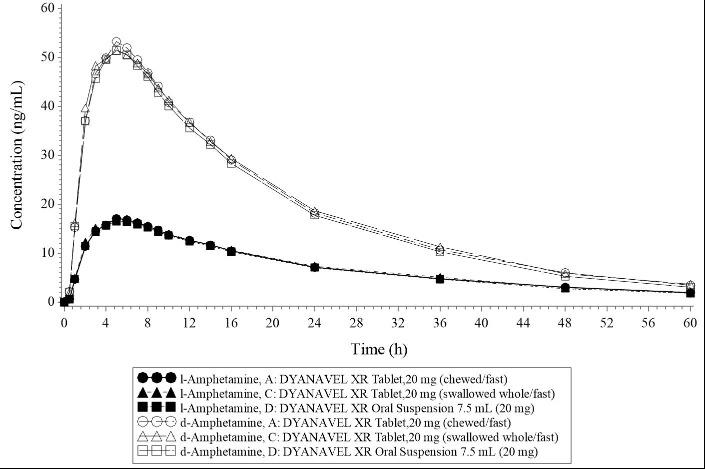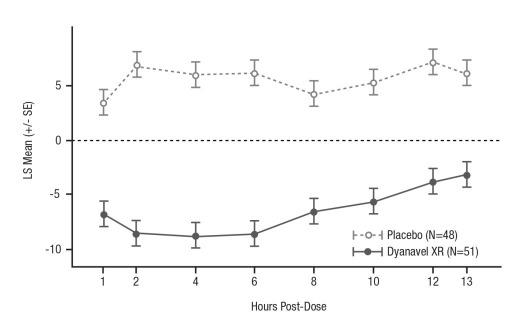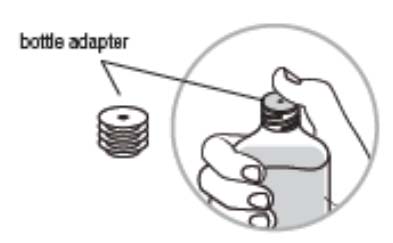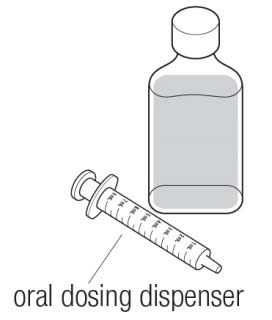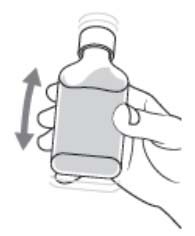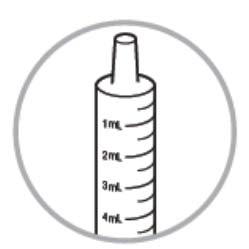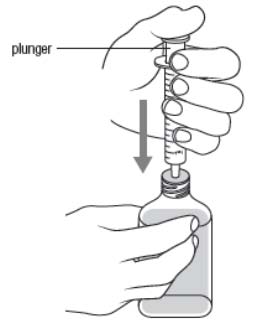 DRUG LABEL: Dyanavel XR
NDC: 24478-102 | Form: SUSPENSION, EXTENDED RELEASE
Manufacturer: NextWave Pharmaceuticals, Inc
Category: prescription | Type: HUMAN PRESCRIPTION DRUG LABEL
Date: 20260224
DEA Schedule: CII

ACTIVE INGREDIENTS: AMPHETAMINE 2.5 mg/1 mL
INACTIVE INGREDIENTS: ANHYDROUS CITRIC ACID; GLYCERIN; METHYLPARABEN; MODIFIED CORN STARCH (1-OCTENYL SUCCINIC ANHYDRIDE); POLYSORBATE 80; POVIDONE; POLYVINYL ACETATE; PROPYLPARABEN; SODIUM LAURYL SULFATE; SODIUM POLYSTYRENE SULFONATE; SUCRALOSE; TRIACETIN; XANTHAN GUM

HIGHLIGHTS OF PRESCRIBING INFORMATION

These highlights do not include all the information needed to use DYANAVEL® XR safely and effectively. See full prescribing information for DYANAVEL XR.
DYANAVEL® XR (amphetamine) extended-release oral suspension, CII
DYANAVEL® XR (amphetamine) extended-release tablets, for oral use, CII
Initial U.S. Approval: 1960

WARNING: ABUSE, MISUSE, AND ADDICTION

See full prescribing information for complete boxed warning.
DYANAVEL XR has a high potential for abuse and misuse, which can lead to the development of a substance use disorder, including addiction. Misuse and abuse of CNS stimulants, including DYANAVEL XR, can result in overdose and death (5.1, 9.2, 10):

- Before prescribing DYANAVEL XR, assess each patient’s risk for abuse, misuse, and addiction.
- Educate patients and their families about these risks, proper storage of the drug, and proper disposal of any unused drug.
- Throughout treatment, reassess each patient’s risk and frequently monitor for signs and symptoms of abuse, misuse, and addiction.

RECENT MAJOR CHANGES

Indications and Usage (1) | 09/2025
Warnings and Precautions (5.5) | 09/2025

1 INDICATIONS AND USAGE

DYANAVEL XR is a central nervous system (CNS) stimulant indicated for the treatment of Attention Deficit Hyperactivity Disorder (ADHD) in patients 6 years and older (1)

Limitations of Use

The use of DYANAVEL XR is not recommended in pediatric patients younger than 6 years of age because they had higher plasma exposure and a higher incidence of adverse reactions (e.g., weight loss) than patients 6 years and older at the same dosage (5.5, 8.4).

2 DOSAGE AND ADMINISTRATION

- Recommended starting dosage is 2.5 mg or 5 mg once daily in the morning (2.2)
- Dosage may be increased in increments of 2.5 mg to 10 mg per day every 4 to 7 days up to a maximum daily dose of 20 mg (2.2)
- May be taken with or without food (2.3)
- Extended-release oral suspension: Shake bottle before administering (2.3)
- Extended-release tablets: May be chewed or swallowed whole (2.3)
- DYANAVEL XR oral suspension can be substituted with DYANAVEL XR tablets on a milligram per milligram basis (2.4)
- Do not substitute for other amphetamine products on a milligram-per-milligram basis, because of different amphetamine salt compositions and differing pharmacokinetic profiles (2.4)

3 DOSAGE FORMS AND STRENGTHS

- Extended-release oral suspension: containing 2.5 mg amphetamine base equivalents per mL (3)
- Extended-release tablets: 5 mg (functionally scored), 10 mg, 15 mg, 20 mg (3)

4 CONTRAINDICATIONS

- Known hypersensitivity to amphetamine products or other ingredients in DYANAVEL XR (4)
- Use of monoamine oxidase inhibitor (MAOI) or within 14 days of the last MAOI dose (4, 7.1)

5 WARNINGS AND PRECAUTIONS

- Risks to Patients with Serious Cardiac Disease: Avoid use in patients with known structural cardiac abnormalities, cardiomyopathy, serious cardiac arrhythmia, coronary artery disease, or other serious cardiac disease (5.2)
- Increased Blood Pressure and Heart Rate: Monitor blood pressure and pulse. (5.3)
- Psychiatric Adverse Reactions: Prior to initiating DYANAVEL XR, screen patients for risk factors for developing a manic episode. If new psychotic or manic symptoms occur, consider discontinuing DYANAVEL XR (5.4)
- Long-Term Suppression of Growth in Pediatric Patients: Closely monitor growth (height and weight) in pediatric patients. Pediatric patients not growing or gaining height or weight as expected may need to have their treatment interrupted (5.5)
- Peripheral Vasculopathy, including Raynaud’s phenomenon: Careful observation for digital changes is necessary during DYANAVEL XR treatment. Further clinical evaluation (e.g., rheumatology referral) may be appropriate for patients who develop signs or symptoms of peripheral vasculopathy (5.6)
- Serotonin Syndrome: Increased risk when co-administered with serotonergic agents (e.g., SSRIs, SNRIs, triptans), but also during overdosage situations. If it occurs, discontinue DYANAVEL XR and initiate supportive treatment (5.7).
- Motor and Verbal Tics, and Worsening of Tourette’s Syndrome: Before initiating DYANAVEL XR, assess the family history and clinically evaluate patients for tics or Tourette’s syndrome. Regularly monitor patients for the emergence or worsening of tics or Tourette’s syndrome. Discontinue treatment if clinically appropriate. (5.8)

6 ADVERSE REACTIONS

Most common adverse reactions observed with amphetamine products: dry mouth, anorexia, weight loss, abdominal pain, nausea, insomnia, restlessness, emotional lability, dizziness, tachycardia (6.1)

To report SUSPECTED ADVERSE REACTIONS, contact Tris Pharma, Inc. at 1-732-940-0358 or FDA at 1-800-FDA-1088 or www.fda.gov/medwatch.

7 DRUG INTERACTIONS

- Acidifying and Alkalinizing Agents: Agents that alter urinary pH can alter blood levels of amphetamine. Acidifying agents can decrease amphetamine blood levels, while alkalinizing agents can increase amphetamine blood levels. Adjust DYANAVEL XR dosage accordingly (2.5, 7.1)

8 USE IN SPECIFIC POPULATIONS

- Pregnancy: May cause fetal harm (8.1)
- Lactation: Breastfeeding not recommended (8.2)

FULL PRESCRIBING INFORMATION

WARNING: ABUSE, MISUSE, AND ADDICTION

DYANAVEL XR has a high potential for abuse and misuse, which can lead to the development of a substance use disorder, including addiction. Misuse and abuse of CNS stimulants, including DYANAVEL XR, can result in overdose and death [see Overdosage (10)], and this risk is increased with higher doses or unapproved methods of administration, such as snorting or injection.
Before prescribing DYANAVEL XR, assess each patient’s risk for abuse, misuse, and addiction. Educate patients and their families about these risks, proper storage of the drug, and proper disposal of any unused drug. Throughout DYANAVEL XR treatment, reassess each patient’s risk of abuse, misuse, and addiction and frequently monitor for signs and symptoms of abuse, misuse, and addiction [see Warnings and Precautions (5.1), Drug Abuse and Dependence (9.2)].

1 INDICATIONS AND USAGE

DYANAVEL XR is indicated for the treatment of Attention Deficit Hyperactivity Disorder (ADHD) in patients 6 years and older [see Clinical Studies (14)].

Limitations of Use

The use of DYANAVEL XR is not recommended in pediatric patients younger than 6 years of age because they had higher plasma exposure and a higher incidence of adverse reactions (e.g., weight loss) than patients 6 years and older at the same dosage [see Warnings and Precautions (5.5), Use in Specific Populations (8.4)].

2 DOSAGE AND ADMINISTRATION

2.1 Pretreatment Screening

Prior to treating patients with DYANAVEL XR, assess:

- for the presence of cardiac disease (i.e., perform a careful history, family history of sudden death or ventricular arrhythmia, and physical exam) [see Warnings and Precautions (5.2)].
- the family history and clinically evaluate patients for motor or verbal tics or Tourette’s syndrome before initiating DYANAVEL XR [see Warnings and Precautions (5.8)].

2.2 Recommended Dosage

The recommended starting dosage is 2.5 mg or 5 mg once daily in the morning. The dosage may be increased in increments of 2.5 mg to 10 mg per day every 4 to 7 days based on clinical response. The maximum recommended dosage is 20 mg once daily.

2.3 Administration Information

Administer DYANAVEL XR orally once daily in the morning with or without food.

DYANAVEL XR Extended-Release Oral Suspension

Instruct patients to read the “Instructions for Use” for complete administration instructions.

- Ensure that the bottle adapter is firmly inserted into the bottle and do not remove once inserted.
- Shake the bottle of DYANAVEL XR extended-release oral suspension well before every administration.
- Use with the oral dosing dispenser provided by the pharmacist.

DYANAVEL XR Extended-Release Tablets

- May be chewed or swallowed whole [see Clinical Pharmacology (12.3)].
- The 5 mg extended-release tablet is functionally scored and may be divided into equal halves (2.5 mg) at the score line.

2.4 Switching from Other Amphetamine Products

DYANAVEL XR extended-release oral suspension can be substituted with DYANAVEL XR extended-release tablets on a milligram-per-milligram basis [see Clinical Pharmacology (12.3)].

If switching from other amphetamine products, discontinue that treatment, and titrate with DYANAVEL XR using the above titration schedule. Do not substitute for other amphetamine products on a milligram-per-milligram basis, because of different amphetamine salt compositions and differing pharmacokinetic profiles [see Description (11), Clinical Pharmacology (12.3)].

2.5 Dosage Modifications due to Drug Interactions

Agents that alter urinary pH can impact urinary excretion and alter blood levels of amphetamine. Acidifying agents (e.g., ascorbic acid) decrease blood levels, while alkalinizing agents (e.g., sodium bicarbonate) increase blood levels. Adjust DYANAVEL XR dosage accordingly [see Drug Interactions (7.1)].

3 DOSAGE FORMS AND STRENGTHS

DYANAVEL XR (amphetamine) extended-release oral suspension:

- Extended-release oral suspension contains 2.5 mg amphetamine base equivalents per mL.

DYANAVEL XR (amphetamine) extended-release tablets:

- 5 mg: Off-white, speckled, caplet shaped tablet with ‘5’ debossed on one side and functionally scored on the other side
- 10 mg: Off-white, speckled, diamond shaped tablet with ‘10’ debossed on one side and plain on the other side
- 15 mg: Off-white, speckled, triangle shaped tablet with ‘15’ debossed on one side and plain on the other side
- 20 mg: Off-white, speckled, oval shaped tablet with ‘20’ debossed on one side and plain on the other side

All strengths are expressed in terms of amphetamine base equivalents.

4 CONTRAINDICATIONS

DYANAVEL XR is contraindicated:

- In patients known to be hypersensitive to amphetamine, or other components of DYANAVEL XR. Hypersensitivity reactions such as angioedema and anaphylactic reactions have been reported in patients treated with other amphetamine products [see Adverse Reactions (6)].
- Patients taking monoamine oxidase inhibitors (MAOIs), or within 14 days of stopping MAOIs (including MAOIs such as linezolid or intravenous methylene blue), because of an increased risk of hypertensive crisis [see Warnings and Precautions (5.7), Drug Interactions (7.1)].

5 WARNINGS AND PRECAUTIONS

5.1 Abuse, Misuse, and Addiction

DYANAVEL XR has a high potential for abuse and misuse. The use of DYANAVEL XR exposes individuals to the risks of abuse and misuse, which can lead to the development of a substance use disorder, including addiction. DYANAVEL XR can be diverted for non-medical use into illicit channels or distribution [see Drug Abuse and Dependence (9.2)]. Misuse and abuse of CNS stimulants, including DYANAVEL XR, can result in overdose and death [see Overdosage (10)], and this risk is increased with higher doses and or unapproved methods of administration, such as snorting or injection.
Before prescribing DYANAVEL XR, assess each patient’s risk for abuse, misuse, and addiction. Educate patients and their families about these risks and proper disposal of any unused drug. Advise patients to store DYANAVEL XR in a safe place, preferably locked, and instruct patients to not give DYANAVEL XR to anyone else. Throughout DYANAVEL XR treatment, reassess each patient’s risk of abuse, misuse, and addiction and frequently monitor for signs and symptoms of abuse, misuse, and addiction.

5.2 Risks for Patients with Serious Cardiac Disease

Sudden death has been reported in patients with structural cardiac abnormalities or other serious cardiac disease who were treated with CNS stimulants at the recommended ADHD dosages.

Avoid DYANAVEL XR use in patients with known structural cardiac abnormalities, cardiomyopathy, serious cardiac arrhythmia, coronary artery disease, or other serious cardiac disease.

5.3 Increased Blood Pressure and Heart Rate

CNS stimulants cause an increase in blood pressure (mean increase about 2 to 4 mm Hg) and heart rate (mean increase about 3 to 6 bpm).

Monitor all DYANAVEL XR-treated patients for potential tachycardia and hypertension.

5.4 Psychiatric Adverse Reactions

Exacerbation of Pre-existing Psychosis

CNS stimulants may exacerbate symptoms of behavior disturbance and thought disorder in patients with a pre-existing psychotic disorder.

Induction of a Manic Episode in Patients with Bipolar Disease

CNS stimulants may induce a manic or mixed episode in patients with bipolar disorder. Prior to initiating DYANAVEL XR treatment, screen patients for risk factors for developing a manic episode (e.g., comorbid or history of depressive symptoms or a family history of suicide, bipolar disorder, or depression).

New Psychotic or Manic Symptoms

CNS stimulants, at the recommended dosage, may cause psychotic or manic symptoms (e.g., hallucinations, delusional thinking, or mania) in patients without prior history of psychotic illness or mania. In a pooled analysis of multiple short-term, placebo-controlled studies of CNS stimulants, psychotic or manic symptoms occurred in approximately 0.1% of CNS stimulant-treated patients compared to 0% of placebo-treated patients. If such symptoms occur, consider discontinuing DYANAVEL XR.

5.5 Long-Term Suppression of Growth in Pediatric Patients

DYANAVEL XR is not approved for use and is not recommended in pediatric patients below 6 years of age [see Use in Specific Populations (8.4)].

CNS stimulants have been associated with weight loss and slowing of growth rate in pediatric patients. Closely monitor growth (weight and height) in DYANAVEL XR-treated pediatric patients treated with CNS stimulants.

Pediatric patients who are not growing or gaining height or weight as expected may need to have their treatment interrupted.

5.6 Peripheral Vasculopathy, including Raynaud's Phenomenon

CNS stimulants, including DYANAVEL XR, used to treat ADHD are associated with peripheral vasculopathy, including Raynaud's phenomenon. Signs and symptoms are usually intermittent and mild; however, sequelae have included digital ulceration and/or soft tissue breakdown. Effects of peripheral vasculopathy, including Raynaud's phenomenon, were observed in post-marketing reports and at the therapeutic dosage of CNS stimulants in all age groups throughout the course of treatment. Signs and symptoms generally improved after dosage reduction or discontinuation of the CNS stimulant.

Careful observation for digital changes is necessary during DYANAVEL XR treatment. Further clinical evaluation (e.g., rheumatology referral) may be appropriate for DYANAVEL XR-treated patients who develop signs or symptoms of peripheral vasculopathy.

5.7 Serotonin Syndrome

Serotonin syndrome, a potentially life-threatening reaction, may occur when amphetamines are used in combination with other drugs that affect the serotonergic neurotransmitter systems such as monoamine oxidase inhibitors (MAOIs), selective serotonin reuptake inhibitors (SSRIs), serotonin norepinephrine reuptake inhibitors (SNRIs), triptans, tricyclic antidepressants, fentanyl, lithium, tramadol, tryptophan, buspirone, and St. John’s Wort [see Drug Interactions (7.1)]. The co-administration with cytochrome P450 2D6 (CYP2D6) inhibitors may also increase the risk with increased exposure to DYANAVEL XR. In these situations, consider an alternative non-serotonergic drug or an alternative drug that does not inhibit CYP2D6 [see Drug Interactions (7.1)].

Serotonin syndrome symptoms may include mental status changes (e.g., agitation, hallucinations, delirium, and coma), autonomic instability (e.g., tachycardia, labile blood pressure, dizziness, diaphoresis, flushing, hyperthermia), neuromuscular symptoms (e.g., tremor, rigidity, myoclonus, hyperreflexia, incoordination), seizures, and/or gastrointestinal symptoms (e.g., nausea, vomiting, diarrhea).

Concomitant use of DYANAVEL XR with MAOI drugs is contraindicated [see Contraindications (4)].

Discontinue treatment with DYANAVEL XR and any concomitant serotonergic agents immediately if symptoms of serotonin syndrome occur, and initiate supportive symptomatic treatment. If concomitant use of DYANAVEL XR with other serotonergic drugs or CYP2D6 inhibitors is clinically warranted, initiate DYANAVEL XR with lower doses, monitor patients for the emergence of serotonin syndrome during drug initiation or titration, and inform patients of the increased risk for serotonin syndrome.

5.8 Motor and Verbal Tics, and Worsening of Tourette’s Syndrome

CNS stimulants, including amphetamine, have been associated with the onset or exacerbation of motor and verbal tics. Worsening of Tourette’s syndrome has also been reported [see Adverse Reactions (6.2)].

Before initiating DYANAVEL XR, assess the family history and clinically evaluate patients for tics or Tourette’s syndrome. Regularly monitor DYANAVEL XR-treated patients for the emergence or worsening of tics or Tourette’s syndrome, and discontinue treatment if clinically appropriate.

6 ADVERSE REACTIONS

The following adverse reactions are discussed in greater detail in other sections of the labeling:

- Abuse, Misuse, and Addiction [see Boxed Warning, Warnings and Precautions (5.1), and Drug Abuse and Dependence (9.2, 9.3)]
- Hypersensitivity to amphetamine, or other components of DYANAVEL XR [see Contraindications (4)]
- Hypertensive Crisis When Used Concomitantly with Monoamine Oxidase Inhibitors [see Contraindications (4) and Drug Interactions (7.1)]
- Risks to Patients with Serious Cardiac Disease [see Warnings and Precautions (5.2)]
- Increased Blood Pressure and Heart Rate [see Warnings and Precautions (5.3)]
- Psychiatric Adverse Reactions [see Warnings and Precautions (5.4)]
- Long-Term Suppression of Growth in Pediatric Patients [see Warnings and Precautions (5.5)]
- Peripheral Vasculopathy, including Raynaud's phenomenon [see Warnings and Precautions (5.6)]
- Serotonin Syndrome [see Warnings and Precautions (5.7)]
- Motor and Verbal Tics, and Worsening of Tourette’s Syndrome [see Warnings and Precautions (5.8)]

6.1 Clinical Trials Experience

Because clinical trials are conducted under widely varying conditions, adverse reaction rates observed in the clinical trials of a drug cannot be directly compared to rates in the clinical trials of another drug and may not reflect the rates observed in clinical practice.

Adverse Reactions in Studies with Other Amphetamine Products in Pediatric Patients and Adults with ADHD

Cardiovascular: Palpitations, tachycardia, elevation of blood pressure, sudden death, myocardial infarction. There have been isolated reports of cardiomyopathy associated with chronic amphetamine use.

Central Nervous System: Psychotic episodes at recommended doses, overstimulation, restlessness, irritability, euphoria, dyskinesia, dysphoria, depression, tremor, tics, aggression, anger, logorrhea.

Eye Disorders: Vision blurred, mydriasis.

Gastrointestinal: Dryness of the mouth, unpleasant taste, diarrhea, constipation, other gastrointestinal disturbances. Anorexia and weight loss may occur as undesirable effects.

Allergic: Urticaria, rash, hypersensitivity reactions including angioedema and anaphylaxis. Serious skin rashes, including Stevens-Johnson syndrome and toxic epidermal necrolysis have been reported.

Endocrine: Impotence, changes in libido.

Skin: Alopecia.

Adverse Reactions in Studies with DYANAVEL XR in Pediatric Patients with ADHD

There is limited experience with DYANAVEL XR in controlled trials. Based on this limited experience, the adverse reaction profile of DYANAVEL XR appears similar to other amphetamine extended-release products. The most common (≥2% in the DYANAVEL XR group and greater than placebo) adverse reactions reported in the Phase 3 controlled study conducted with DYANAVEL XR extended-release oral suspension in 108 patients with ADHD (aged 6 to 12 years) were: epistaxis, allergic rhinitis, and upper abdominal pain.

Table 1. Common Adverse Reactions Occurring in ≥2% of Patients on DYANAVEL XR Extended-Release Oral Suspension and Greater than Placebo During the Double Blind Phase.

Preferred Term | DYANAVEL XR (N=52) | Placebo (N=48)
Respiratory, thoracic and mediastinal disorders
Epistaxis | 3.8% | 0%
Rhinitis allergic | 3.8% | 0%
Gastrointestinal disorders
Abdominal pain upper | 3.8% | 2.1%

6.2 Postmarketing Experience

The following adverse reactions have been identified during post approval use of other amphetamine products. Because these reactions are reported voluntarily from a population of uncertain size, it is not possible to reliably estimate their frequency or establish a causal relationship to drug exposure.

Allergic: urticaria, rash, hypersensitivity reactions including angioedema and anaphylaxis. Serious skin rashes, including Stevens-Johnson Syndrome and toxic epidermal necrolysis have been reported

Cardiovascular: palpitations, sudden death, myocardial infarction. There have been isolated reports of cardiomyopathy associated with chronic amphetamine use

Central Nervous System: restlessness, irritability, euphoria, dyskinesia, dysphoria, depression, tremor, aggression, anger, logorrhea, and paresthesia (including formication), motor and verbal tics

Endocrine: impotence, changes in libido, frequent or prolonged erections

Eye Disorders: vision blurred, mydriasis

Gastrointestinal: unpleasant taste, constipation, intestinal ischemia, and other gastrointestinal disturbances

Musculoskeletal, Connective Tissue, and Bone Disorders: rhabdomyolysis

Psychiatric Disorders: dermatillomania, bruxism

Skin: alopecia

Vascular Disorders: Raynaud’s phenomenon

7 DRUG INTERACTIONS

7.1 Drugs Having Clinically Important Interactions with Amphetamines

Table 2. Drugs having clinically important interactions with amphetamines.

MAO Inhibitors (MAOI)
Clinical Impact | MAOI antidepressants slow amphetamine metabolism, increasing amphetamines effect on the release of norepinephrine and other monoamines from adrenergic nerve endings causing headaches and other signs of hypertensive crisis. Toxic neurological effects and malignant hyperpyrexia can occur, sometimes with fatal results.
Intervention | Do not administer DYANAVEL XR concomitantly or within 14 days following administration of MAOI [see Contraindications (4) and Warnings and Precautions (5.7)].
Serotonergic Drugs
Clinical Impact | The concomitant use of DYANAVEL XR and serotonergic drugs increases the risk of serotonin syndrome.
Intervention | Initiate with lower doses and monitor patients for signs and symptoms of serotonin syndrome, particularly during DYANAVEL XR initiation or dosage increase. If serotonin syndrome occurs, discontinue DYANAVEL XR and the concomitant serotonergic drug(s) [see Warnings and Precautions (5.7)].
CYP2D6 Inhibitors
Clinical Impact | The concomitant use of DYANAVEL XR and CYP2D6 inhibitors may increase the exposure of DYANAVEL XR compared to the use of the drug alone and increase the risk of serotonin syndrome.
Intervention | Initiate with lower doses and monitor patients for signs and symptoms of serotonin syndrome particularly during DYANAVEL XR initiation and after a dosage increase. If serotonin syndrome occurs, discontinue DYANAVEL XR and the CYP2D6 inhibitor [see Warnings and Precautions (5.7), Overdosage (10)].
Alkalinizing Agents (Urinary and Gastrointestinal)
Clinical Impact | Increase blood levels and potentiate the action of amphetamine.
Intervention | Co-administration of DYANAVEL XR and gastrointestinal or urinary alkalinizing agents should be avoided.
Acidifying Agents (Urinary and Gastrointestinal)
Clinical Impact | Lower blood levels and efficacy of amphetamines.
Intervention | Increase dose based on clinical response.
Tricyclic Antidepressants
Clinical Impact | May enhance the activity of tricyclic or sympathomimetic agents causing striking and sustained increases in the concentration of d-amphetamine in the brain; cardiovascular effects can be potentiated.
Intervention | Monitor frequently and adjust or use alternative therapy based on clinical response.

7.2 Drug/Laboratory Test Interactions

Amphetamines can cause a significant elevation in plasma corticosteroid levels. This increase is greatest in the evening. Amphetamines may interfere with urinary steroid determinations.

8 USE IN SPECIFIC POPULATIONS

8.1 Pregnancy

Pregnancy Exposure Registry

There is a pregnancy exposure registry that monitors pregnancy outcomes in women exposed to DYANAVEL XR during pregnancy. Healthcare providers are encouraged to register patients by calling the National Pregnancy Registry for Psychostimulants at 1-866-961-2388 or visiting online at https://womensmentalhealth.org/clinical-and-research-programs/pregnancyregistry/othermedications/.

Risk Summary

There are limited published data on the use of amphetamines in pregnant women. These data are insufficient to determine a drug-associated risk of major congenital malformations or miscarriage. Adverse pregnancy outcomes, including premature delivery and low birth weight, have been seen in infants born to mothers dependent on amphetamines. No effects on morphological development were observed in embryo-fetal development studies with oral administration of amphetamine to rats and rabbits during organogenesis at doses that are approximately 3 and 16 times, respectively, the maximum recommended human dose (MRHD) of 20 mg/day (as base equivalents) on a mg/m^2 basis, given to adults. However, long-term neurochemical and behavioral effects have been reported in published animal developmental studies using clinically relevant doses of amphetamine [see Data]. In the U.S. general population, the estimated background risk of major birth defects and miscarriage in clinically recognized pregnancies is 2% to 4% and 15% to 20%, respectively.

Clinical Considerations

Fetal/Neonatal adverse reactions

Amphetamines, such as DYANAVEL XR, may cause vasoconstriction, including vasoconstriction of placental blood vessels, and may increase the risk for intrauterine growth restriction. In addition, amphetamines can stimulate uterine contractions increasing the risk of premature delivery. Premature delivery and low birth weight infants have been reported in amphetamine-dependent mothers.

Monitor infants born to mothers taking amphetamines for symptoms of withdrawal, such as feeding difficulties, irritability, agitation, and excessive drowsiness.

Data

Animal Data

Amphetamine (d- to l- enantiomer ratio of 3:1) had no apparent effects on embryofetal morphological development or survival when orally administered to pregnant rats and rabbits throughout the period of organogenesis at doses of up to 6 and 16 mg/kg/day, respectively. These doses are approximately 3 and 16 times, respectively, the MRHD of 20 mg/day (as base equivalents) on a mg/m^2 basis, given to adults. Fetal malformations and death have been reported in mice following parenteral administration of d-amphetamine doses of 50 mg/kg/day (approximately 12 times the MRHD) given to adults on a mg/m^2 basis or greater to pregnant animals. Administration of these doses was also associated with severe maternal toxicity.

A number of studies in rodents indicate that prenatal or early postnatal exposure to amphetamine

(d- or d, l-), at doses similar to those used clinically, can result in long-term neurochemical and behavioral alterations. Reported behavioral effects include learning and memory deficits, altered locomotor activity, and changes in sexual function.

8.2 Lactation

Risk Summary

Based on limited case reports in published literature, amphetamine (d- or d, l-) is present in human milk, at relative infant doses of 2% to 13.8% of the maternal weight-adjusted dosage and a milk/plasma ratio ranging between 1.9 and 7.5. There are no reports of adverse effects on the breastfed infant and no effects on milk production. However, long term neurodevelopmental effects on infants from stimulant exposure are unknown. Because of the potential for serious adverse reactions in a breastfed infant, advise patients that breastfeeding is not recommended during treatment with DYANAVEL XR.

8.4 Pediatric Use

The safety and effectiveness of DYANAVEL XR have not been established in pediatric patients below the age of 6 years.

In studies evaluating extended-release amphetamine products, patients 4 to <6 years of age had higher systemic amphetamine exposures than those observed in older pediatric patients at the same dosage. Pediatric patients 4 to <6 years of age also had a higher incidence of adverse reactions, including weight loss.

The safety and effectiveness have been established in pediatric patients with ADHD ages 6 to 17 years [see Adverse Reactions (6.1), Clinical Pharmacology (12), and Clinical Studies (14)].

Long-Term Growth Suppression

Growth should be monitored during treatment with stimulants, including DYANAVEL XR, and pediatric patients who are not growing or gaining weight as expected may need to have their treatment interrupted [see Warnings and Precautions (5.5)].

8.5 Geriatric Use

DYANAVEL XR has not been studied in the geriatric population.

9 DRUG ABUSE AND DEPENDENCE

9.1 Controlled Substance

DYANAVEL XR contains amphetamine, a Schedule II controlled substance.

9.2 Abuse

DYANAVEL XR has a high potential for abuse and misuse which can lead to the development of a substance use disorder, including addiction [see Warnings and Precautions (5.1)]. DYANAVEL XR can be diverted for non-medical use into illicit channels or distribution.

Abuse is the intentional non-therapeutic use of a drug, even once, to achieve a desired psychological or physiological effect. Misuse is the intentional use, for therapeutic purposes, of a drug by an individual in a way other than prescribed by a health care provider or for whom it was not prescribed. Drug addiction is a cluster of behavioral, cognitive, and physiological phenomena that may include a strong desire to take the drug, difficulties in controlling drug use (e.g., continuing drug use despite harmful consequences, giving a higher priority to drug use than other activities and obligations), and possible tolerance or physical dependence.

Misuse and abuse of amphetamine may cause increased heart rate, respiratory rate, or blood pressure; sweating; dilated pupils; hyperactivity; restlessness; insomnia; decreased appetite; loss of coordination; tremors; flushed skin; vomiting; and/or abdominal pain. Anxiety, psychosis, hostility, aggression, and suicidal or homicidal ideation have also been observed with CNS stimulants abuse and/or misuse. Misuse and abuse of CNS stimulants, including DYANAVEL XR, can result in overdose and death [see Overdosage (10)], and this risk is increased with higher doses or unapproved methods of administration, such as snorting or injection.

9.3 Dependence

Physical Dependence

DYANAVEL XR may produce physical dependence. Physical dependence is a state that develops as a result of physiological adaptation in response to repeated drug use, manifested by withdrawal signs and symptoms after abrupt discontinuation or a significant dose reduction of a drug.

Withdrawal signs and symptoms after abrupt discontinuation or dose reduction following prolonged use of CNS stimulants including DYANAVEL XR include dysphoric mood; depression; fatigue; vivid, unpleasant dreams; insomnia or hypersomnia; increased appetite; and psychomotor retardation or agitation.

Tolerance

DYANAVEL XR may produce tolerance. Tolerance is a physiological state characterized by a reduced response to a drug after repeated administration (i.e., a higher dose of a drug is required to produce the same effect that was once obtained at a lower dose).

10 OVERDOSAGE

Clinical Effects of Overdose

Overdose of CNS stimulants is characterized by the following sympathomimetic effects:

- Cardiovascular effects including tachyarrhythmias, and hypertension or hypotension. Vasospasm, myocardial infarction, or aortic dissection may precipitate sudden cardiac death. Takotsubo cardiomyopathy may develop.
- CNS effects including psychomotor agitation, confusion, and hallucinations. Serotonin syndrome, seizures, cerebral vascular accidents, and coma may occur.
- Life-threatening hyperthermia (temperatures greater than 104°F) and rhabdomyolysis may develop.

Overdose Management

Consider the possibility of multiple drug ingestion. The pharmacokinetic profile of DYANAVEL XR should be considered when treating patients with overdose. D-amphetamine is not dialyzable. Consider contacting the Poison Help line (1-800-222-1222) or a medical toxicologist for additional overdose management recommendations.

11 DESCRIPTION

DYANAVEL XR (amphetamine) extended-release oral suspension and DYANAVEL XR (amphetamine) extended-release tablets contain amphetamine, a CNS stimulant, in a 3.2:1 ratio of d- to l- amphetamine.

There are three active ingredients: amphetamine (complexed with sodium polystyrene sulfonate), dextroamphetamine sulfate and amphetamine aspartate. The dosage strengths are expressed in terms of amphetamine base.

DYANAVEL XR contains both immediate-release and extended-release components.

Structural Formula:

C9H13N MW 135.21

Active Ingredients:

DYANAVEL XR extended-release oral suspension 2.5 mg/mL:

- Each 1 mL contains 2 mg of amphetamine (in a 3.2 to 1 ratio of d- to l-amphetamine complexed with sodium polystyrene sulfonate), and 0.5 mg amphetamine (present as 0.5 mg of amphetamine aspartate and 0.3 mg of dextroamphetamine sulfate).

DYANAVEL XR extended-release tablets:

- Each 5 mg strength tablet contains 4 mg of amphetamine (in a 3.2 to 1 ratio of d- to l-amphetamine complexed with sodium polystyrene sulfonate), and 1 mg of amphetamine (present as 1 mg of amphetamine aspartate and 0.7 mg of dextroamphetamine sulfate).
- Each 10 mg strength tablet contains 8 mg of amphetamine (in a 3.2 to 1 ratio of d- to l-amphetamine complexed with sodium polystyrene sulfonate), and 2 mg of amphetamine (present as 2 mg amphetamine aspartate and 1.4 mg dextroamphetamine sulfate).
- Each 15 mg strength tablet contains 12 mg of amphetamine (in a 3.2 to 1 ratio of d- to l-amphetamine complexed with sodium polystyrene sulfonate), and 3 mg of amphetamine (present as 3 mg amphetamine aspartate and 2 mg dextroamphetamine sulfate).
- Each 20 mg strength tablet contains 16 mg of amphetamine (in a 3.2 to 1 ratio of d- to l-amphetamine complexed with sodium polystyrene sulfonate), and 4 mg of amphetamine (present as 4 mg amphetamine aspartate and 2.7 mg dextroamphetamine sulfate).

DYANAVEL XR extended-release oral suspension and DYANAVEL XR extended-release tablets are intended for oral administration.

Inactive Ingredients:

DYANAVEL XR extended-release oral suspension: anhydrous citric acid, bubblegum flavor, glycerin, methylparaben, modified starch, polysorbate 80, povidone, polyvinyl acetate, propylparaben, sodium lauryl sulfate, sodium polystyrene sulfonate, sucralose, triacetin and xanthan gum.

DYANAVEL XR extended-release tablets: bubblegum flavor, crospovidone, guar gum, magnesium stearate, mannitol, microcrystalline cellulose, polyvinyl acetate, povidone, silicon dioxide, sodium polystyrene sulfonate, sucralose, talc, triacetin and xanthan gum.

12 CLINICAL PHARMACOLOGY

12.1 Mechanism of Action

Amphetamines are non-catecholamine sympathomimetic amines with CNS stimulant activity. The mode of therapeutic action in ADHD is not known.

12.2 Pharmacodynamics

Amphetamines block the reuptake of norepinephrine and dopamine into the presynaptic neuron and increase the release of these monoamines into the extra neuronal space.

12.3 Pharmacokinetics

Absorption

Extended-Release Oral Suspension

Following a single 18.8 mg dose of DYANAVEL XR extended-release oral suspension in 29 healthy adult subjects under fasting conditions in a crossover study, the median (range) time to peak plasma concentrations (Tmax) for both d- and l- isomers of amphetamine were 4 (2 to 7) hours after dosing. Peak concentrations (Cmax) of d- and l-amphetamine were 102% and 106%, respectively, of the Cmax of immediate-release (IR) mixed amphetamine salts (MAS) tablets. The relative bioavailability of DYANAVEL XR compared with an equal dose of IR MAS tablets is 106% for d- and 111% for l-amphetamine.

Following a single 18.8 mg dose of DYANAVEL XR extended-release oral suspension in 28 healthy adult subjects in a crossover study under fasting conditions, the median (range) time to peak plasma concentrations (Tmax) were about 4 (2 to 7) hours and 5 (3 to 7) hours for d- and l-amphetamine, respectively. Peak concentration (Cmax) was 93% and 94%, respectively, of the Cmax of extended release (ER) MAS capsules. The relative bioavailability of DYANAVEL XR compared with an equal dose of ER MAS capsules is 94% for both d- and l-amphetamine.

Figure 1. Mean d- and l-Amphetamine Plasma Concentration-Time Profile Following Administration of a Single Dose (18.8 mg amphetamine base) of DYANAVEL XR Extended-Release Oral Suspension and MAS ER Under Fasting Conditions

Extended-Release Tablet

Following a single 20 mg dose of DYANAVEL XR extended-release tablets (swallowed whole) to 36 healthy adults under fasted conditions in a crossover study, the median (range) time to peak plasma concentration (Tmax) for both d- and l-amphetamine, were 5.0 (2 to 9) hours after dosing. Peak concentrations (Cmax) for both d- and l-amphetamine, were 101% of the Cmax of DYANAVEL XR oral suspension. The relative bioavailability of DYANAVEL XR tablets compared with an equal dose of DYANAVEL XR oral suspension, for d- and l-amphetamine, were 105% and 106%, respectively.

Dyanavel XR extended-release tablets chewed or swallowed whole under fasted conditions did not significantly affect exposure and Tmax.

Figure 2. Mean Plasma d- and l-Amphetamine Concentration-Time Profiles for DYANAVEL XR Extended-Release Tablet and DYANAVEL XR Extended-Release Oral Suspension

Effect of Food

Extended-Release Oral Suspension

Ingestion of 18.8 mg of DYANAVEL XR extended-release oral suspension with a high-fat meal increased the average Cmax of both isomers of DYANAVEL XR by about 2%, decreased the AUC of d- and l-amphetamine by 5.7% and 7.4%, respectively. A delay of Tmax by approximately 1 hour was observed for both isomers.

Extended-Release Tablet

Ingestion of 20 mg DYANAVEL XR extended-release tablets with a high-fat meal decreased the average Cmax of both isomers of amphetamine by about 3%, decreased AUC of d- and l-amphetamine by about 4.0% and 7.3%, respectively. Median Tmax was not delayed for either isomer.

Elimination

The mean plasma terminal elimination half-lives of d- and l-amphetamine were 12.4 hours and 15.1 hours, respectively, following a single 18.8 mg dose of DYANAVEL XR extended-release oral suspension.

The mean plasma terminal elimination half-lives of d- and l-amphetamine were 13.5 hours and 17.3 hours, respectively, following a single 20 mg dose of DYANAVEL XR extended-release tablets.

Metabolism

Amphetamine is reported to be oxidized at the 4 position of the benzene ring to form 4‑hydroxyamphetamine, or on the side chain A or B carbons to form alpha-hydroxy-amphetamine or norephedrine, respectively. Norephedrine and 4-hydroxy-amphetamine are both active and each is subsequently oxidized to form 4-hydroxy-norephedrine. Alpha-hydroxy-amphetamine undergoes deamination to form phenylacetone, which ultimately forms benzoic acid and its glucuronide and the glycine conjugate hippuric acid. Although the enzymes involved in amphetamine metabolism have not been clearly defined, CYP2D6 is known to be involved with formation of 4-hydroxy-amphetamine. Because CYP2D6 is genetically polymorphic, population variations in amphetamine metabolism are a possibility.

Excretion

With normal urine pH, approximately half of an administered dose of amphetamine is recoverable in urine as derivatives of alpha-hydroxy-amphetamine and approximately another 30%-40% of the dose is recoverable in urine as amphetamine itself.

Specific Populations

Pediatric Patients

Following a single 10 mg dose of DYANAVEL XR extended-release oral suspension in pediatric subjects with ADHD (aged 6 to 12 years) under fasting conditions, peak plasma concentrations of d-and l-amphetamine occurred at a median time of 3.9 and 4.5 hours after dosing, respectively. The mean plasma terminal elimination half-lives of d- and l-amphetamine were 10.4 hours and 12.1 hours, respectively.

Patients with Hepatic or Renal Impairment

No specific studies have been conducted to evaluate the effect of renal impairment or hepatic impairment on the PK after DYANAVEL XR administration. However, urinary recovery of amphetamine has been reported to range from 1% to 75%, depending on urinary pH, with the remaining fraction of the dose hepatically metabolized. Consequently, both hepatic and renal dysfunctions have the potential to inhibit the elimination of amphetamine and result in prolonged exposures.

Drug Interaction Studies

CYP Enzymes

In vitro experiments with human microsomes indicate minor inhibition of CYP2D6 by amphetamine and minor inhibition of CYP1A2, 2D6, and 3A4 by one or more metabolites. However, because of the probability of auto-inhibition and the lack of information on the concentration of these metabolites relative to in vivo concentrations, no predications regarding the potential for amphetamine or its metabolites to inhibit the metabolism of other drugs by CYP isozymes in vivo can be made.

Urine pH Modulators

Because amphetamine has a pKa of 9.9, urinary recovery of amphetamine is highly dependent on pH and urine flow rates. Alkaline urine pH results in less ionization and reduced renal elimination; acidic pH and high flow rates result in increased renal elimination with clearances greater than glomerular filtration rates, indicating the involvement of active secretion. In addition, any decrease in amphetamine’s metabolism that might occur due to drug interactions or genetic polymorphisms is more likely to be clinically significant when renal elimination is decreased [see Drug Interactions (7.1)].

Alcohol Effect

There is no in vivo study conducted for the effect of alcohol on drug exposure. An in vitro dissolution study on DYANAVEL XR extended-release oral suspension showed alcohol-induced dose dumping potential in the presence of 40% alcohol. A similar study on the DYANAVEL XR extended-release tablets showed no alcohol-induced dose dumping in the presence of 40% alcohol. Dose dumping was not observed in the presence of 5%, 10%, or 20% alcohol concentrations for either product.

13 NONCLINICAL TOXICOLOGY

13.1 Carcinogenesis, Mutagenesis, Impairment of Fertility

Carcinogenesis

No evidence of carcinogenicity was found in studies in which d, l-amphetamine (enantiomer ratio of 1:1) was administered to mice and rats in the diet for 2 years at doses of up to 30 mg/kg/day in male mice, 19 mg/kg/day in female mice, and 5 mg/kg/day in male and female rats. These doses are approximately 7, 5, and 2 times, respectively, the maximum recommended human dose of 20- mg/day (as base equivalents) given to adults, on a mg/m^2 basis.

Mutagenesis

Amphetamine, in the enantiomer ratio (d- to l- ratio of approximately 3:1), was not clastogenic in the mouse bone marrow micronucleus test in vivo and was negative when tested in the E. coli component of the Ames test in vitro. d, l-Amphetamine (1:1 enantiomer ratio) has been reported to produce a positive response in the mouse bone marrow micronucleus test, an equivocal response in the Ames test, and negative responses in the in vitro sister chromatid exchange and chromosomal aberration assays.

Impairment of Fertility

Amphetamine, in the enantiomer ratio (d- to l- ratio of approximately 3:1), did not adversely affect fertility or early embryonic development in the rat at doses of up to 20 mg/kg/day [approximately 10 times the maximum recommended human dose of 20 mg/day (as base equivalents) given to adults on a mg/m^2 basis].

13.2 Animal Toxicology and/or Pharmacology

Acute administration of high doses of amphetamine (d- or d, l-) has been shown to produce long-lasting neurotoxic effects, including irreversible nerve fiber damage, in rodents. The significance of these findings to humans is unknown.

14 CLINICAL STUDIES

The efficacy of DYANAVEL XR extended-release oral suspension was evaluated in a laboratory classroom study conducted in 108 pediatric patients (aged 6 to 12 years) with ADHD. The study began with an open-label dose optimization period (5 weeks) with an initial DYANAVEL XR dose of 2.5 or 5 mg once daily in the morning. The dose could be titrated weekly in increments of 2.5 to 10 mg until an optimal dose or the maximum dose of 20 mg/day was reached. Subjects then entered a 1-week randomized, double-blind treatment with the individually optimized dose of DYANAVEL XR or placebo. At the end of the week, school teachers and raters evaluated the attention and behavior of the subjects in a laboratory classroom using the Swanson, Kotkin, Agler, M-Flynn, and Pelham (SKAMP) rating scale. SKAMP is a 13-item teacher-rated scale that assesses manifestations of ADHD in a classroom setting. Each item is rated on a 7-point impairment scale.

The primary efficacy endpoint was change from pre-dose in the SKAMP-Combined score at 4 hours post-dosing. The key secondary efficacy parameters were onset and duration of clinical effect. The change scores from pre-dose SKAMP-Combined scores at post-dose time points (1, 2, 4, 6, 8, 10, 12 and 13 hours) were used to evaluate the key secondary efficacy parameters. Results from the double-blind, placebo-controlled week of the study are summarized in Table 3 and Figure 3.

SKAMP-Combined change scores from pre-dose demonstrated a statistically significant improvement at all time points (1, 2, 4, 6, 8, 10, 12, 13 hours) post-dosing with DYANAVEL XR compared to placebo.

Table 3. Summary of Primary Efficacy Results in Pediatric Patients (6 to 12 years) with ADHD

Study Number | Treatment Group | Primary Efficacy Measure: SKAMP-Combined Score
 |  | Mean Pre-dose Score (SD) | LS Mean Change from Pre-Dose at 4 Hours Post-Dosing (SE) | Placebo-subtracted Difference a (95% CI)
Study 1 | DYANAVEL XR Extended-Release Oral Suspension | 17.3 (8.88) | -8.8 (1.14) | -14.8 (-17.9, -11.6)
 | Placebo | 15.5 (7.35) | 6.0 (1.19) | --
SD: standard deviation; SE: standard error; LS Mean: least-squares mean; CI: confidence interval.
a Difference (drug minus placebo) in least-squares mean change from pre-dose.

Figure 3. LS Mean Change from Pre-dose in SKAMP-Combined Score after Treatment with DYANAVEL XR Extended-Release Oral Suspension or Placebo in Pediatric Patients (6 to 12 years) with ADHD

16 HOW SUPPLIED/STORAGE AND HANDLING

How Supplied

DYANAVEL XR (amphetamine) extended-release oral suspension: The concentration is 2.5 mg/mL amphetamine base equivalents and is supplied as light beige to tan viscous suspension with bubblegum flavor in bottles of 60 mL (NDC 24478-102-02) and 464 mL (NDC 24478-102-01).

The product is provided in a carton.

60 mL carton contains two oral dispensers and two bottle adapters.
464 mL carton contains four oral dispensers and four bottle adapters.

DYANAVEL XR (amphetamine) extended-release tablets: Supplied in bottles (that contain a desiccant) with child-resistant closure as 5 mg, 10 mg, 15 mg, and 20 mg strengths.

- 5 mg DYANAVEL XR extended-release tablet is functionally scored and is available as an off-white, speckled, caplet shaped tablet with 5 debossed on one side and scored on the other side, supplied in bottles of 30 (NDC 24478-106-01).
- 10 mg DYANAVEL XR extended-release tablet is available as an off-white, speckled, diamond shaped tablet with 10 debossed on one side and plain on the other side, supplied in bottles of 30 (NDC 24478-108-01).
- 15 mg DYANAVEL XR extended-release tablet is available as an off-white, speckled, triangle shaped tablet with 15 debossed on one side and plain on the other side, supplied in bottles of 30 (NDC 24478-109-01).
- 20 mg DYANAVEL XR extended-release tablet is available as an off-white, speckled, oval shaped tablet with 20 debossed on one side and plain on the other side, supplied in bottles of 30 (NDC 24478-110-01).

Storage and Handling

Dispense in a tight, light-resistant container with a child-resistant closure.

Store at 20° to 25°C (68° to 77°F); excursions permitted from 15º to 30ºC (59º to 86ºF) [see USP Controlled Room Temperature].

DYANAVEL XR extended-release oral suspension: The pharmacist should insert the bottle adapter firmly into the neck of the bottle and provide the oral dosing dispenser to the patient when dispensing this product.

17 PATIENT COUNSELING INFORMATION

Advise the patient to read the FDA-approved patient labeling (Medication Guide and Instructions for Use).

Abuse, Misuse, and Addiction

Educate patients and their families about the risks of abuse, misuse, and addiction of DYANAVEL XR, which can lead to overdose and death, and proper disposal of any unused drug [see Warnings and Precautions (5.1), Drug Abuse and Dependence (9.2), Overdosage (10)]. Advise patients to store DYANAVEL XR in a safe place, preferably locked, and instruct patients to not give DYANAVEL XR to anyone else.

Dosage and Administration Instructions

Provide the following instructions on administration to the patient [see Dosage and Administration (2.3)]:

DYANAVEL XR extended-release oral suspension

- Use with the oral dosing dispenser provided by the pharmacist.
- Ensure that the bottle adapter has been firmly inserted into the bottle by the pharmacist. Do not remove the bottle adapter once it has been inserted into the bottle.
- Shake the bottle before each dose.

DYANAVEL XR extended-release tablets

- Tablets may be chewed or swallowed whole.

Risks to Patients with Serious Cardiac Disease

Advise patients that there are potential risks to patients with serious cardiac disease, including sudden death, with DYANAVEL XR use. Instruct patients to contact a healthcare provider immediately if they develop symptoms such as exertional chest pain, unexplained syncope, or other symptoms suggestive of cardiac disease [see Warnings and Precautions (5.2)].

Increased Blood Pressure and Heart Rate

Instruct patients and their caregivers that DYANAVEL XR can cause elevations of their blood pressure and pulse rate [see Warnings and Precautions (5.3)].

Psychiatric Adverse Reactions

Advise patients and their caregivers that DYANAVEL XR, at recommended doses, may cause psychotic or manic symptoms, even in patients without a prior history of psychotic symptoms or mania [see Warnings and Precautions (5.4)].

Long-Term Suppression of Growth in Pediatric Patients

Advise patients and their caregivers that DYANAVEL XR may cause slowing of growth and weight loss [see Warnings and Precautions (5.5)].

Circulation Problems in Fingers and Toes [Peripheral vasculopathy, including Raynaud’s phenomenon]

Instruct patients and their caregivers beginning treatment with DYANAVEL XR about the risk of peripheral vasculopathy, including Raynaud's phenomenon, and associated signs and symptoms: fingers or toes may feel numb, cool, painful, and/or may change color from pale, to blue, to red.

Instruct patients and their caregivers to report to their physician any new numbness, pain, skin color change, or sensitivity to temperature in fingers or toes.

Instruct patients and their caregivers to call their physician immediately with any signs of unexplained wounds appearing on fingers or toes while taking DYANAVEL XR.

Further clinical evaluation (e.g., rheumatology referral) may be appropriate for certain patients [see Warnings and Precautions (5.6)].

Serotonin Syndrome

Caution patients and their caregivers about the risk of serotonin syndrome with concomitant use of DYANAVEL XR and other serotonergic drugs including SSRIs, SNRIs, triptans, tricyclic antidepressants, fentanyl, lithium, tramadol, tryptophan, buspirone, St. John’s Wort, and with drugs that impair metabolism of serotonin (in particular MAOIs, both those intended to treat psychiatric disorders and also others such as linezolid [see Contraindications (4), Warnings and Precautions (5.7) and Drug Interactions (7.1)]. Advise patients to contact their healthcare provider or report to the emergency room if they experience signs or symptoms of serotonin syndrome.

Motor and Verbal Tics, and Worsening of Tourette’s Syndrome

Advise patients that motor and verbal tics and worsening of Tourette’s Syndrome may occur during treatment with DYANAVEL XR. Instruct patients to notify their healthcare provider if emergence of new tics or worsening of tics or Tourette’s syndrome occurs [see Warnings and Precautions (5.8)].

Concomitant Medications

Advise patients and their caregivers to notify their physicians if they are taking, or plan to take, any prescription or over-the-counter drugs because there is a potential for interactions [see Drug Interactions (7.1)].

Pregnancy Registry

Advise patients and their caregivers that there is a pregnancy exposure registry that monitors pregnancy outcomes in women exposed to DYANAVEL XR during pregnancy [see Use in Specific Populations (8.1)].

Pregnancy

Advise patients and their caregivers to notify their healthcare provider if they become pregnant or intend to become pregnant during treatment with DYANAVEL XR. Advise patients of the potential fetal effects from the use of DYANAVEL XR during pregnancy [see Use in Specific Populations (8.1)].

Lactation

Advise women not to breastfeed if they are taking DYANAVEL XR [see Use in Specific Populations (8.2)].

Alcohol

Advise patients to avoid alcohol while taking DYANAVEL XR. Consumption of alcohol while taking

DYANAVEL XR may result in a more rapid release of the dose of amphetamine [see Clinical Pharmacology (12.3)].

Manufactured by:

Tris Pharma, Inc.
Monmouth Junction, NJ 08852

LB8684
Rev. 04

MEDICATION GUIDE

DYANAVEL® XR (dī-an-uh-vel)
(amphetamine) extended-release oral suspension, CII

DYANAVEL® XR (dī-an-uh-vel)

(amphetamine) extended-release tablets, CII

What is the most important information I should know about DYANAVEL XR?

DYANAVEL XR may cause serious side effects, including:

- Abuse, misuse, and addiction. DYANAVEL XR has a high chance for abuse and misuse and may lead to substance use problems, including addiction. Misuse and abuse of DYANAVEL XR, other amphetamine containing medicines, and methylphenidate containing medicines, can lead to overdose and death. The risk of overdose and death is increased with higher doses of DYANAVEL XR or when it is used in ways that are not approved, such as snorting or injection.

- Your healthcare provider should check you or your child’s risk for abuse, misuse, and addiction before starting, treatment with DYANAVEL XR and will monitor you or your child during treatment.
- DYANAVEL XR may lead to physical dependence after prolonged use, even if taken as directed by your healthcare provider.
- Do not give DYANAVEL XR to anyone else. See “What is DYANAVEL XR?” for more information.
- Keep DYANAVEL XR in a safe place and properly dispose of any unused medicine. See “How should I store DYANAVEL XR?” for more information.
- Tell your healthcare provider if you or your child have ever abused or been dependent on alcohol, prescription medicines, or street drugs.

- Risks for people with serious heart disease. Sudden death has happened in people who have heart defects or other serious heart disease.

Your healthcare provider should check you or your child carefully for heart problems before starting treatment with DYANAVEL XR. Tell your healthcare provider if you or your child have any heart problems, heart disease, or heart defects.

Call your healthcare provider or go to the nearest hospital emergency room right away if you or your child has any signs of heart problems such as chest pain, shortness of breath, or fainting during treatment with DYANAVEL XR.

- Increased blood pressure and heart rate.
  Your healthcare provider should check you or your child’s blood pressure and heart rate regularly during treatment with DYANAVEL XR.
- Mental (psychiatric) problems, including:
  - new or worse behavior and thought problems
  - new or worse bipolar illness
  - new psychotic symptoms (such as hearing voices, or seeing or believing things that are not real) or new manic symptoms

Tell your healthcare provider about any mental problems you or your child have, or about a family history of suicide, bipolar illness, or depression.

Call your healthcare provider right away if you or your child have any new or worsening mental symptoms or problems during treatment with DYANAVEL XR, especially hearing voices, seeing or believing things that are not real, or new manic symptoms.

What is DYANAVEL XR?

DYANAVEL XR is a central nervous system (CNS) stimulant prescription medicine used for the treatment of Attention Deficit Hyperactivity Disorder (ADHD) in people 6 years of age and older. DYANAVEL XR may help increase attention and decrease impulsiveness and hyperactivity in people with ADHD.

DYANAVEL XR is not recommended for use in children under 6 years of age with ADHD.

DYANAVEL XR is a federally controlled substance (CII) because it contains amphetamine that can be a target for people who abuse prescription medicines or street drugs. Keep DYANAVEL XR in a safe place to protect it from theft. Never give your DYANAVEL XR to anyone else, because it may cause death or harm them. Selling or giving away DYANAVEL XR may harm others and is against the law.

Do not take DYANAVEL XR if you or your child are:

- allergic to amphetamine products or any of the ingredients in DYANAVEL XR. See the end of this Medication Guide for a complete list of ingredients in DYANAVEL XR.
- taking, or have taken within the past 14 days a medicine called a monoamine oxidase inhibitor (MAOI), including the antibiotic linezolid and the intravenous medicine methylene blue. Ask your healthcare provider or pharmacist if you are not sure if you or your child take any of these medicines.

Before taking DYANAVEL XR tell your healthcare provider about all medical conditions, including if you or your child:

- have heart problems, heart disease, heart defects, or high blood pressure
- have mental problems including psychosis, mania, bipolar illness, or depression
- have circulation problems in fingers and toes
- have or had repeated movements or sounds (tics) or Tourette’s syndrome, or have a family history of tics or Tourette’s syndrome
- are pregnant or plan to become pregnant. It is not known if DYANAVEL XR will harm the unborn baby.
  - There is a pregnancy registry for females who are exposed to DYANAVEL XR during pregnancy. The purpose of the registry is to collect information about the health of females exposed to DYANAVEL XR and their baby. If you or your child becomes pregnant during treatment with DYANAVEL XR, talk to your healthcare provider about registering with the National Pregnancy Registry for Psychostimulants at 1-866-961-2388.
- are breastfeeding or plan to breastfeed. DYANAVEL XR passes into breast milk. You or your child should not breastfeed during treatment with DYANAVEL XR.

Tell your healthcare provider about all of the medicines that you or your child takes, including prescription and over-the-counter medicines, vitamins, and herbal supplements.

DYANAVEL XR and some medicines may interact with each other and cause serious side effects. Sometimes the doses of other medicines will need to be adjusted during treatment with DYANAVEL XR.

Especially tell your healthcare provider if you or your child take:

- MAOIs
- serotonin norepinephrine reuptake inhibitors (SNRIs)
- tricyclic antidepressants
- lithium
- tryptophan
- selective serotonin reuptake inhibitors (SSRIs)
- medicines used to treat migraine headaches called triptans
- fentanyl
- tramadol
- buspirone
- St. John’s Wort

Your healthcare provider will decide whether DYANAVEL XR can be taken with other medicines. Do not start any new medicine during treatment with DYANAVEL XR without talking to your healthcare provider first.

How should I take DYANAVEL XR?

- See the detailed “Instructions for Use” for information on how to give a dose of DYANAVEL XR extended-release oral suspension.

- Take DYANAVEL XR exactly as prescribed by your healthcare provider.
- Your healthcare provider may change the dose if needed.
- Take DYANAVEL XR 1 time each day in the morning.
- DYANAVEL XR can be taken with or without food.
- DYANAVEL XR extended-release tablets may be chewed or swallowed whole.
- DYANAVEL XR extended-release 5 mg tablets are scored and can be divided into equal parts at the score line.

If you or your child take too much DYANAVEL XR, call your healthcare provider or Poison Help line at 1-800-222-1222, or go to the nearest hospital emergency room right away.

What should I avoid during treatment with DYANAVEL XR?

You should avoid drinking alcohol during treatment with DYANAVEL XR.

What are possible side effects of DYANAVEL XR?

DYANAVEL XR may cause serious side effects, including:

- See “What is the most important information I should know about DYANAVEL XR?”
- Slowing of growth (height and weight) in children. Children should have their height and weight checked often during treatment with DYANAVEL XR. Your healthcare provider may stop your child’s DYANAVEL XR treatment if they are not growing or gaining weight as expected.
- Circulation problems in fingers and toes (peripheral vasculopathy, including Raynaud’s phenomenon). Signs and symptoms may include:
  - fingers or toes may feel numb, cool, painful
  - fingers or toes may change color from pale, to blue, to red

Tell your healthcare provider if you or your child have numbness, pain, skin color change, or sensitivity to temperature in your fingers or toes.

Call your healthcare provider right away if you or your child have any signs of unexplained wounds appearing on fingers or toes during treatment with DYANAVEL XR.

- New or worsening tics or worsening Tourette’s syndrome. Tell your healthcare provider if you or your child get any new or worsening tics or worsening Tourette’s syndrome during treatment with DYANAVEL XR.

- Serotonin Syndrome. This problem may happen when DYANAVEL XR is taken with certain other medicines and may be life-threatening. Stop taking DYANAVEL XR and call your healthcare provider or go to the nearest hospital emergency room if you get symptoms of serotonin syndrome which may include:
  - agitation
  - confusion
  - fast heart beat
  - dizziness
  - flushing
  - tremors, stiff muscles, or muscle twitching
  - seizures
  - seeing or hearing things that are not real (hallucination)
  - coma
  - changes in blood pressure
  - sweating
  - high body temperature (hyperthermia)
  - loss of coordination
  - nausea, vomiting, diarrhea

The most common side effects of DYANAVEL XR include:

- dry mouth
- decreased appetite
- weight loss
- stomach pain
- nausea
- trouble sleeping
- restlessness
- extreme mood changes
- dizziness
- increased heart rate

These are not all of the possible side effects of DYANAVEL XR.

Call your doctor for medical advice about side effects. You may report side effects to FDA at 1-800-FDA-1088.

How should I store DYANAVEL XR?

- Store DYANAVEL XR at room temperature between 68°F to 77°F (20°C to 25°C).
- Store DYANAVEL XR in a safe place, like a locked cabinet.
- Dispose of remaining, unused, or expired DYANAVEL XR by a medicine take-back program at a U.S. Drug Enforcement Administration (DEA) authorized collection site. If no take-back program or DEA authorized collector is available, mix DYANAVEL XR with an undesirable, nontoxic substance such as dirt, cat litter, or used coffee grounds to make it less appealing to children and pets. Place the mixture in a container such as a sealed plastic bag and throw away DYANAVEL XR in the household trash. Visit www.fda.gov/drugdisposal for additional information on disposal of unused medicines.

Keep DYANAVEL XR and all medicines out of the reach of children.

General information about the safe and effective use of DYANAVEL XR.

Medicines are sometimes prescribed for purposes other than those listed in the Medication Guide. Do not use DYANAVEL XR for a condition for which it has not been prescribed. Do not give DYANAVEL XR to other people, even if they have the same symptoms. It may harm them and it is against the law. You can ask your healthcare provider or pharmacist for information about DYANAVEL XR that is written for healthcare professionals.

What are the ingredients in DYANAVEL XR?
DYANAVEL XR extended-release oral suspension:
Active Ingredients: amphetamine, dextroamphetamine sulfate and amphetamine aspartate.
Inactive Ingredients: anhydrous citric acid, bubblegum flavor, glycerin, methylparaben, modified starch, polysorbate 80, povidone, polyvinyl acetate, propylparaben, sodium lauryl sulfate, sodium polystyrene sulfonate, sucralose, triacetin and xanthan gum.
DYANAVEL XR extended-release tablets:
Active Ingredients: amphetamine, dextroamphetamine sulfate and amphetamine aspartate.
Inactive Ingredients: bubblegum flavor, crospovidone, guar gum, magnesium stearate, mannitol, microcrystalline cellulose, polyvinyl acetate, povidone, silicon dioxide, sodium polystyrene sulfonate, sucralose, talc, triacetin and xanthan gum.
Manufactured by: Tris Pharma, Inc., Monmouth Junction, NJ 08852
For more information about DYANAVEL XR go to www.dyanavelxr.com or call 1-732-940-0358.

This Medication Guide has been approved by the U.S. Food and Drug Administration. Revised: 09/2025

Instructions for Use

DYANAVEL® XR (dī-an-uh-vel)
(amphetamine)
extended-release oral suspension, CII

Read this Instructions for Use before taking DYANAVEL XR and each time you get a refill. There may be new information. This leaflet does not take the place of talking with the healthcare provider about your or your child’s medical condition or treatment.

Step 1:

- Check the DYANAVEL XR bottle to make sure that the bottle adapter has been inserted into the bottle by the pharmacist. Do not remove the bottle adapter.
- Check to make sure your pharmacist has given you an oral dosing dispenser.
- Tell your pharmacist if an oral dosing dispenser is not provided or the bottle adapter is missing from the neck of the bottle.

Step 2:

- Shake the bottle well (up and down).

Step 3:

- Check the DYANAVEL XR oral dosing dispenser to find the right dose in milliliters (mL) that you or your child’s healthcare provider has prescribed.

Step 4:

- Place the DYANAVEL XR bottle upright and insert tip of the oral dosing dispenser into the bottle.

Step 5:

- Push the plunger all the way down.

Step 6:

- With the oral dosing dispenser in place, hold the DYANAVEL XR bottle with 1 hand and turn the bottle upside down. Pull the plunger down until the white end of the plunger reaches the number of mLs you need for the prescribed dose.

Step 7:

- Turn the bottle over and place upright on a counter top, then remove the oral dosing dispenser from the bottle adapter.

Step 8:

- Place the tip of the oral dosing dispenser into you or your child’s mouth. Point the tip toward the cheek and slowly push the plunger all the way down to give the DYANAVEL XR dose.

Step 9:

- Put the DYANAVEL XR cap back on the bottle and close tightly.

Step 10:

- Clean the oral dosing dispenser after each use by placing in the dishwasher, or by rinsing with tap water.

How should I store DYANAVEL XR?

- Store DYANAVEL XR at room temperature between 68°F to 77°F (20°C to 25°C).
- Store DYANAVEL XR in a safe place, like a locked cabinet.
- Dispose of remaining, unused, or expired DYANAVEL XR by a medicine take-back program at a U.S. Drug Enforcement Administration (DEA) authorized collection sites such as retail pharmacies, hospital or clinic pharmacies, and law enforcement locations. If no take-back program or DEA authorized collector is available, mix DYANAVEL XR with an undesirable, nontoxic substance such as dirt, cat litter, or used coffee grounds to make it less appealing to children and pets. Place the mixture in a container such as a sealed plastic bag and throw away DYANAVEL XR in the household trash.

Keep DYANAVEL XR and all medicines out of the reach of children.

Manufactured by:
Tris Pharma, Inc.
Monmouth Junction, NJ 08852

For more information about DYANAVEL XR go to www.dyanavelxr.com or call 1-732-940-0358.

This Instructions for Use has been approved by the U.S. Food and Drug Administration Revised: 10/2023

PRINCIPAL DISPLAY PANEL

NDC 24478-102-01

Dyanavel® XR CII
(amphetamine) extended-release oral suspension

2.5 mg/mL

Shake Well Before Use

464 mL Rx only

PRINCIPAL DISPLAY PANEL

NDC 24478-102-02

Dyanavel® XR CII
(amphetamine) extended-release oral suspension

2.5 mg/mL

Shake Well Before Use

60 mL Rx only

PRINCIPAL DISPLAY PANEL

NDC 24478-106-01

Dyanavel®XR CII

(amphetamine) extended-release Tablets

5 mg

May be chewed or swallowed whole.

30 Tablets

Rx only

PRINCIPAL DISPLAY PANEL

NDC 24478-108-01

Dyanavel®XR CII

(amphetamine) extended-release Tablets

10 mg

May be chewed or swallowed whole.

30 Tablets

Rx only

PRINCIPAL DISPLAY PANEL

NDC 24478-109-01

Dyanavel®XR CII

(amphetamine) extended-release Tablets

15 mg

May be chewed or swallowed whole.

30 Tablets

Rx only

PRINCIPAL DISPLAY PANEL

NDC 24478-110-01

Dyanavel® XR CII

(amphetamine) extended-release Tablets

20 mg

May be chewed or swallowed whole.

30 Tablets

Rx only